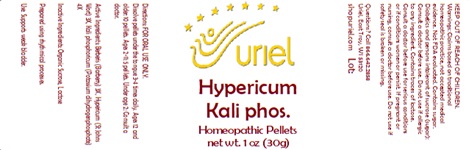 DRUG LABEL: Hypericum Kali Phos.
NDC: 48951-5098 | Form: PELLET
Manufacturer: Uriel Pharmacy Inc
Category: homeopathic | Type: HUMAN OTC DRUG LABEL
Date: 20241203

ACTIVE INGREDIENTS: BERBERIS VULGARIS FRUIT 3 [hp_X]/1 1; HYPERICUM PERFORATUM 3 [hp_X]/1 1; POTASSIUM PHOSPHATE, UNSPECIFIED FORM 4 [hp_X]/1 1
INACTIVE INGREDIENTS: LACTOSE, UNSPECIFIED FORM; SUCROSE

Hypericum Kali Phos. Pellets

INDICATIONS AND USAGE

Directions: FOR ORAL USE ONLY.

DOSAGE AND ADMINISTRATION

Dissolve pellets under the tongue 3-4 times daily. Ages 12 and older: 10 pellets. Ages 2-11: 5 pellets. Under age 2: Consult a doctor.

ACTIVE INGREDIENT

Active Ingredients: Berberis (Barberry) 3X, Hypericum (St Johns Wort) 3X, Kali phosphoricum (Potassium dihydrogenphosphate) 4X

Inactive Ingredients: Organic Sucrose, Lactose

Prepared using rhythmical processes.

PURPOSE

Use: Supports weak bladder.

KEEP OUT OF REACH OF CHILDREN.

WARNINGS

Warnings: Claims based on traditional homeopathic practice, not accepted medical evidence. Not FDA evaluated. Contains sugar. Diabetics and persons intolerant of sucrose (sugar): Consult a doctor before use. Do not use if allergic to any ingredient. Contains traces of lactose. Consult a doctor before use for serious conditions or if conditions worsen or persist. If pregnant or nursing, consult a doctor before use. Do not use if safety seal is broken or missing.

Questions? Call 866 642-2858

Uriel, East Troy, WI 53120

shopuriel.com Lot: